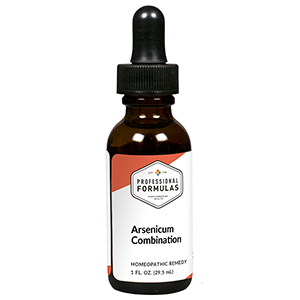 DRUG LABEL: Arsenicum Combination
NDC: 63083-9251 | Form: LIQUID
Manufacturer: Professional Complementary Health Formulas
Category: homeopathic | Type: HUMAN OTC DRUG LABEL
Date: 20190815

ACTIVE INGREDIENTS: SELENICEREUS GRANDIFLORUS STEM 3 [hp_X]/29.5 mL; POTASSIUM CARBONATE 4 [hp_X]/29.5 mL; KALMIA LATIFOLIA LEAF 4 [hp_X]/29.5 mL; ARNICA MONTANA WHOLE 6 [hp_X]/29.5 mL; HAWTHORN LEAF WITH FLOWER 6 [hp_X]/29.5 mL; LACTIC ACID, DL- 6 [hp_X]/29.5 mL; NITROGLYCERIN 6 [hp_X]/29.5 mL; STRYCHNOS IGNATII SEED 6 [hp_X]/29.5 mL; RANUNCULUS BULBOSUS WHOLE 6 [hp_X]/29.5 mL; OXOGLURIC ACID 8 [hp_X]/29.5 mL; ARSENIC TRIOXIDE 8 [hp_X]/29.5 mL; FUMARIC ACID 8 [hp_X]/29.5 mL; BEEF HEART 8 [hp_X]/29.5 mL; BEEF LIVER 8 [hp_X]/29.5 mL; MALIC ACID 8 [hp_X]/29.5 mL; SODIUM DIETHYL OXALACETATE 8 [hp_X]/29.5 mL; STROPHANTHUS HISPIDUS SEED 8 [hp_X]/29.5 mL; NAJA NAJA VENOM 10 [hp_X]/29.5 mL; SPIGELIA ANTHELMIA WHOLE 10 [hp_X]/29.5 mL; ACTIVATED CHARCOAL 12 [hp_X]/29.5 mL; COXSACKIEVIRUS A21 30 [hp_X]/29.5 mL; HUMAN HERPESVIRUS 5 30 [hp_X]/29.5 mL; HUMAN HERPESVIRUS 4 30 [hp_X]/29.5 mL
INACTIVE INGREDIENTS: ALCOHOL; WATER

R251

ACTIVE INGREDIENTS

Cactus grandiflorus 3X
Kali carbonicum 4X
Kalmia latifolia 4X
Arnica montana 6X
Crataegus oxyacantha 6X
L(+) Lacticum acidum 6X
Glonoinum 6X
Ignatia amara 6X
Ranunculus bulbosus 6X
a-Ketoglutaricum acidum 8X
Arsenicum album 8X
Fumaricum acidum 8X
Heart 8X
Liver 8X
Malic acid 8X
Natrum oxalaceticum 8X
Strophanthus hispidus 8X
Naja tripudians 10X
Spigelia anthelmia 10X
Carbo vegetabilis 12X
Coxsackievirus 30X
Cytomegalovirus 30X
Epstein-Barr virus 30X

QUESTIONS

Professional Formulas

PO Box 2034 Lake Oswego, OR 97035

INDICATIONS

For the temporary relief of weakness, exhaustion, restlessness, anxiousness, or muscle pain, spasms, or tightness.*

PURPOSE

*Claims based on traditional homeopathic practice, not accepted medical evidence. Not FDA evaluated.

WARNINGS

Seek medical attention immediately for severe symptoms such as chest pressure or tightness with radiation of the pain to the jaw and down the arm, shortness of breath, or sweating. Keep out of the reach of children. In case of overdose, get medical help or contact a poison control center right away. If pregnant or breastfeeding, ask a healthcare professional before use.

Keep out of the reach of children.

PREGNANCY OR BREAST FEEDING

If pregnant or breastfeeding, ask a healthcare professional before use.

DIRECTIONS

Place drops under tongue 30 minutes before/after meals. Adults and children 12 years and over: Take 10 drops up to 3 times per day. Consult a physician for use in children under 12 years of age.

OTHER INFORMATION

Tamper resistant. If seal is broken, do not use. After opening, close container tightly and store at room temperature away from heat.

INACTIVE INGREDIENTS

40% ethanol, purified water.

LABEL

Est 1985

Professional Formulas

Complementary Health

Arsenicum Combination

Homeopathic Remedy

1 FL. OZ. (29.5 mL)